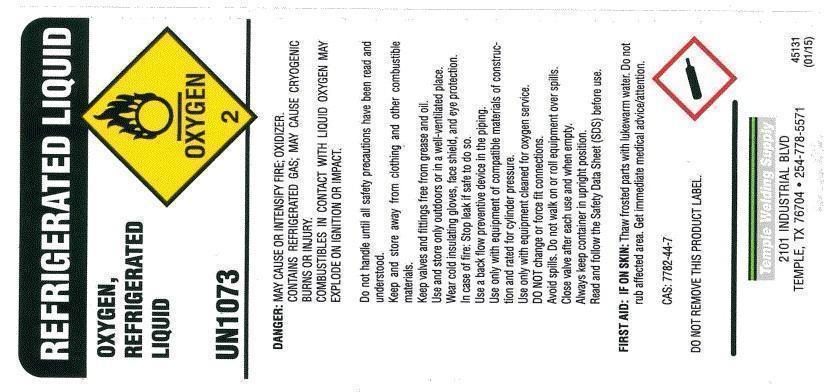 DRUG LABEL: Oxygen
NDC: 11103-001 | Form: GAS
Manufacturer: Temple Industrial Welding Supply Co
Category: prescription | Type: HUMAN PRESCRIPTION DRUG LABEL
Date: 20241010

ACTIVE INGREDIENTS: OXYGEN 990 mL/1 L

Oxygen

PACKAGE LABEL

Refrigerated Liquid
Oxygen,
Refrigerated
Liquid
USP
UN1073
Oxygen, 2
DANGER: MAY CAUSE OR INTENSIFY FIRE; OXIDIZER. CONTAINS REFRIGERATED GAS; MAY CAUSE CRYOGENIC BURNS OR INJURY. COMBUSTIBLES IN CONTACT WITH LIQUID OXYGEN MAY EXPLODE ON IGNITION OR IMPACT. Do not handle until all safety precautions have been read and understood. Keep and store away from clothing and other combustible materials. Keep valves and fittings free from grease and oil. Use and store only outdoors or in a well-ventilated place. Wear cold insulating gloves, face shield, and eye protection. In case of fire: Stop leak if safe to do so. Use a back flow preventive device in the piping. Use only with equipment of compatible materials of construction and rated for cylinder pressure. Use only equipment cleaned for oxygen service. DO NOT change or force fit connections. Avoid spills. Do not walk on or roll equipment over spills. Close valve after each use and when empty. Always keep container in upright position. Read and follow the Safety Data Sheet (SDS) before use

FIRST AID: IF ON SKIN: Thaw frosted parts with lukewarm water. Do not rub affected area. Get immediate medical advice/attention.
CAS: 7782-44-7

Temple Welding Supply
2101 Industrial Blvd
Temple, TX 76704
254-778-5571